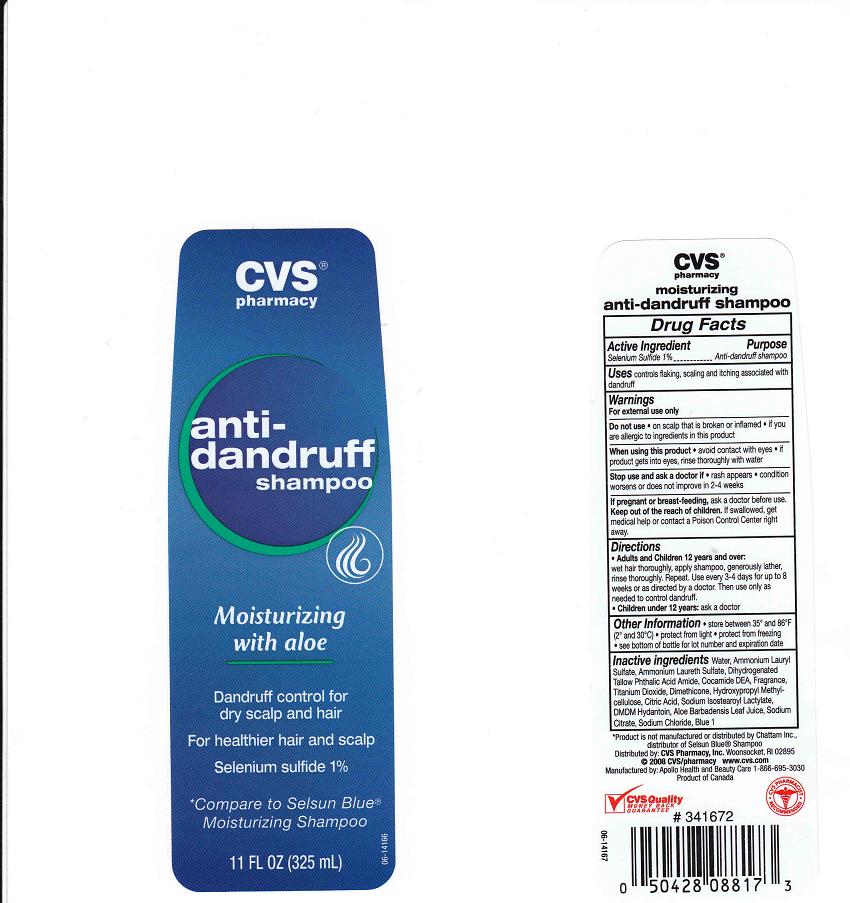 DRUG LABEL: CVS Pharmacy Dandruff
NDC: 59779-611 | Form: SHAMPOO
Manufacturer: CVS Pharmacy Inc
Category: otc | Type: HUMAN OTC DRUG LABEL
Date: 20101015

ACTIVE INGREDIENTS: SELENIUM SULFIDE 1 mL/100 mL
INACTIVE INGREDIENTS: WATER; AMMONIUM LAURYL SULFATE; AMMONIUM LAURETH-2 SULFATE; COCO DIETHANOLAMIDE; TITANIUM DIOXIDE; DIMETHICONE; HYPROMELLOSE 2208 (100 MPA.S); CITRIC ACID MONOHYDRATE; SODIUM ISOSTEAROYL LACTYLATE; DMDM HYDANTOIN; ALOE VERA LEAF; SODIUM CITRATE; SODIUM CHLORIDE; FD&C BLUE NO. 1

Active Ingredient

Selenium Sulfide 1%

Purpose

Anti-Dandruff

Uses

Controls flaking, scaling and itching associated with dandruff

Warnings

For external use only

Do Not Use

- On scalp that is broken or inflamed.
- If you are allergic to ingredients in this product

When using this product

avoid contact with eyes. If contact occurs, rinse with water. For use on color treated or permed hair, rinse thoroughly

Stop using this product and ask doctor if

- rash appears
- condition worsens or does not improve in 2-4 weeks

Keep out of reach of children

In case of accidental ingestion, get medical help or contact a Poison Control Center immediately

If pregnant or breast feeding

ask a doctor before use

Directions

- Adults and children 12 years and over: wet hair thoroughly, apply shampoo, generously lather, rinse thoroughly. Repeat. Use every 3-4 days for up to 8 weeks or as directed by a doctor. Then use only as needed to control dandruff.
- Children under 12 years: ask a doctor

Other Information

- store between 35o and 85o F (2o and 30oC)
- protect from freezing
- see bottom of bottle for lot number and expiration date

Inactive Ingredients

Water (Aqua), Ammonium Lauryl Sulfate, Ammonium Laureth Sulfate, Dihydrogenated Tallow Phthalic Acid Amide, Cocamide DEA, Fragrance (Parfum), Titanium Dioxide, Dimethicone, Hydroxypropyl Methylcellulose, Citric Acid, Sodium Isostearoyl Lactylate, DMDM Hydantoin, Aloe Barbadensis Leaf Juice, Sodium Citrate, Sodium Chloride, Blue 1 (CI 42090)

Package Front and Back Labels

ra11.jpg